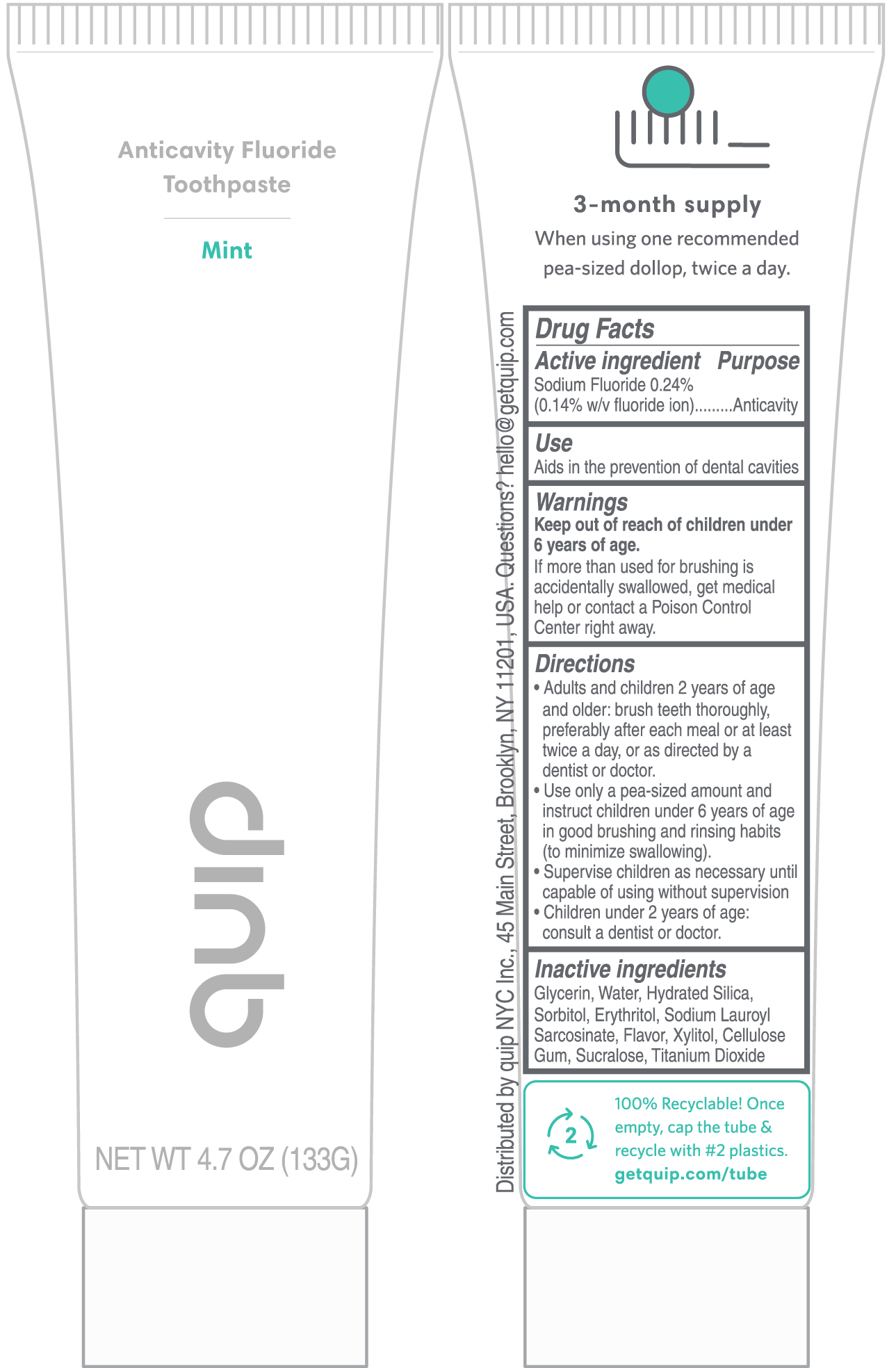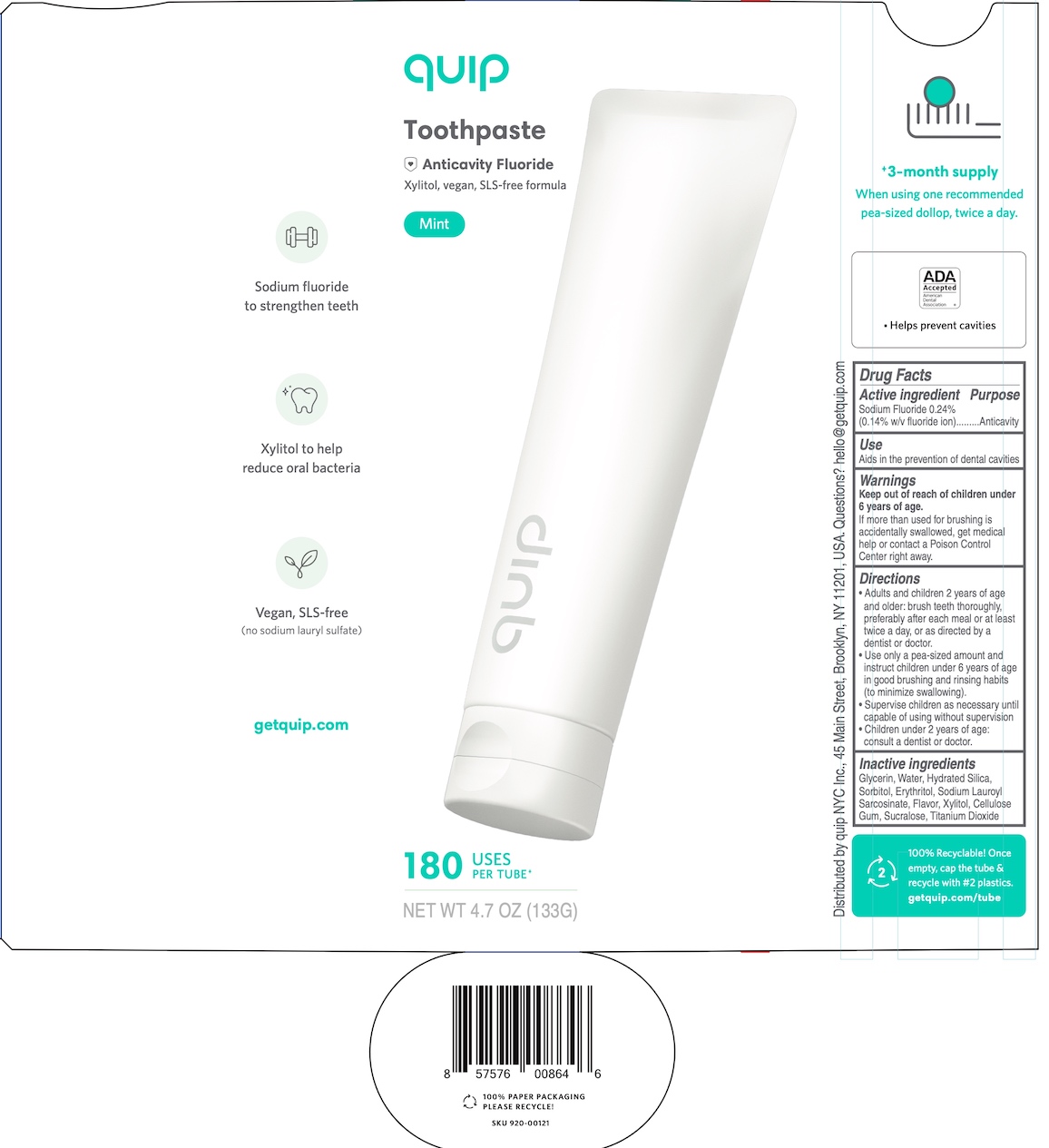 DRUG LABEL: Quip Anticavity
NDC: 69261-006 | Form: PASTE, DENTIFRICE
Manufacturer: Quip NYC Inc.
Category: otc | Type: HUMAN OTC DRUG LABEL
Date: 20250130

ACTIVE INGREDIENTS: SODIUM FLUORIDE 0.24 g/100 g
INACTIVE INGREDIENTS: SODIUM LAUROYL SARCOSINATE; HYDRATED SILICA; GLYCERIN; TITANIUM DIOXIDE; SORBITOL; WATER; SUCRALOSE; XYLITOL; ERYTHRITOL; CARBOXYMETHYLCELLULOSE SODIUM (0.7 CARBOXYMETHYL SUBSTITUTION PER SACCHARIDE; 2300 MPA.S AT 1%)

Quip Anticavity Toothpaste, Mint

Drug Facts

Active ingredient

Sodium fluoride 0.24% (0.14% w/v fluoride ion)

Purpose

Anticavity

Use

Aids in the prevention of dental cavities

Warnings

Keep out of reach of children under 6 years of age.

If more than used for brushing is accidentally swallowed, get medical help or contact a Poison Control Center right away.

Directions

- Adults and children 2 years of age and older: brush teeth thoroughly, preferably after each meal or at least twice a day, or as directed by a dentist or doctor.
- Use only a pea-sized amount and instruct children under 6 years of age in good brushing and rinsing habits (to minimize swallowing).
- Supervise children as necessary until capable of using without supervision
- Children under 2 years of age: consult a dentist or doctor.

Inactive ingredients

Glycerin, Water, Hydrated Silica, Sorbitol, Erythritol, Sodium Lauroyl Sarcosinate, Flavor, Xylitol, Cellulose Gum, Sucralose, Titanium Dioxide

Distributed by: quip NYC Inc., 45 Main Street, Brooklyn, NY 11201, USA

Questions? hello@getquip.com

Carton

quip

Toothpaste

Anticavity Fluoride

Xylitol, vegan, SLS-free formula

Mint

180 USES PER TUBE

NET WT 4.7 OZ (133G)

Tube

Anticavity Fluoride Toothpaste

Mint

quip

NET WT 4.7 OZ (133G)